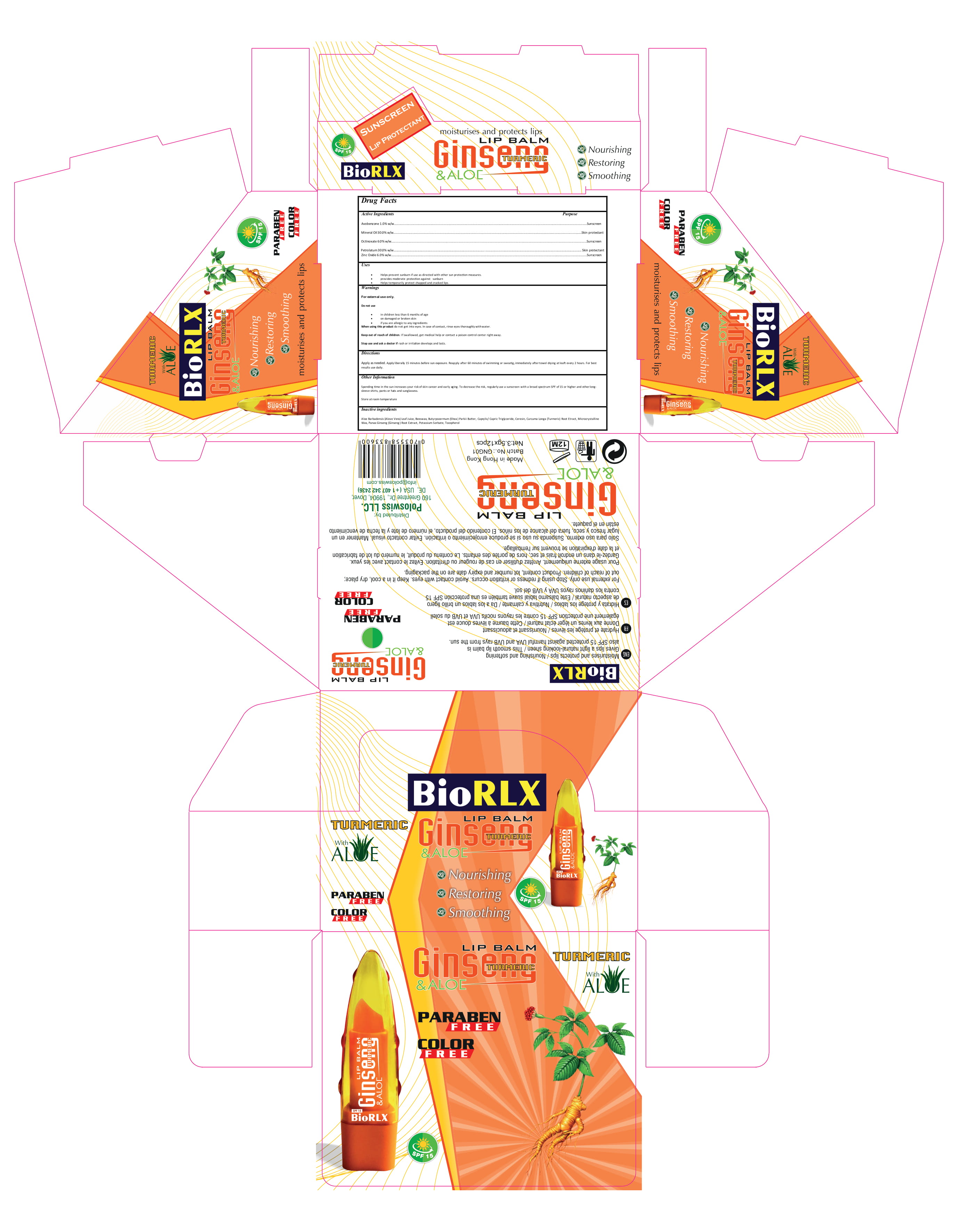 DRUG LABEL: BIORLX LIP BALM GINSENG
NDC: 80554-003 | Form: STICK
Manufacturer: LOTUSA LLC.
Category: otc | Type: HUMAN OTC DRUG LABEL
Date: 20200918

ACTIVE INGREDIENTS: AVOBENZONE 1 g/100 g; OCTINOXATE 6 g/100 g; ZINC OXIDE 6 g/100 g; PETROLATUM 30 g/100 g; MINERAL OIL 30 g/100 g
INACTIVE INGREDIENTS: BUTYROSPERMUM PARKII (SHEA) BUTTER UNSAPONIFIABLES; WHITE WAX; ALOE VERA LEAF; CERESIN; CURCUMA LONGA LEAF; PANAX GINSENG ROOT OIL; TOCOPHEROL; POTASSIUM SORBATE; MICROCRYSTALLINE WAX; MEDIUM-CHAIN TRIGLYCERIDES

a. Avobenzone 1.0%w/w

b. Mineral Oil 30.0%w/w

c. Octinoxate 6.0% w/w

d. Petrolatum 30.0% w/w

e. Zinc Oxide 6.0% w/w

f. Aloe Barbadensis (Alove Vera) Leaf Juice

g. Beeswax

h. Butyrospermum (Shea) Parkii Butter

i.Curcuma Longa (Turmeric) Root Extract

j. Caprylic/ Capric Triglyceride

k. Ceresin

l. Microcrystalline Wax

m. Potassium Sorbate

n. Tocopherol

o. Panax Ginseng (Ginseng) Root Extract

The firm does not add other active or inactive ingredients. Different or additional ingredients may impact the quality and potency of the product.

Active Ingredient(s)

Avobenzone 1.0% w/w Sunscreen
Mineral Oil 30.0% w/w Skin protectant
Octinoxate 6.0% w/w Sunscreen
Petrolatum 30.0% w/w Skin protectant
Zinc Oxide 6.0% w/w Sunscreen

Purpose

Sunscreen, Skin protectant, Lip Balm

Use

Helps prevent sunburn if use as directed with other sun protection measures.
provides moderate protection against sunburn
Helps temporarily protect chapped and cracked lips.

Warnings

For external use only.

Do not use

- in children less than 6 months of age
  on damaged or broken skin
  • if you are allergic to any ingredients

When using this product do not get into eyes. In case of contact, rinse eyes thoroughly with water.
Stop use and ask a doctor if rash or irritation develops and lasts.
Keep out of reach of children. If swallowed, get medical help or contact a Poison Control Center right away.

Stop use and ask a doctor if rash or irritation develops and lasts.

Keep out of reach of children. If swallowed, get medical help or contact a Poison Control Center right away.

Directions

Apply as needed. Apply liberally 15 minutes before sun exposure. Reapply after 60 minutes of swimming or sweatig, immediately after towel drying at leaft every 2 hours. For best results use daily.

Other information

- Spending time in the sun increases your risk of skin cancer and early aging. To decrease the risk, regularly use a sunscreen with a broad spectrum SPF of 15 or higher and other longsleeve shirts, pants or hats and sunglassess.
  Store at room temperature

Inactive ingredients

Aloe Barbadensis (Alove Vera) Leaf Juice, Beeswax, Butyrpsoermum (Shea) Parkii Butter, Caprylic/ Capric Triglyceride, Ceresin, Curcuma Longa (Turmeric) Root Etract, Microcrystalline Wax, Panax Ginseng (Ginseng) Root Extract, Potassium Sorbate, Tocopherol

Package Label - Principal Display Panel

12x3.5 g NDC: 80554-003-01